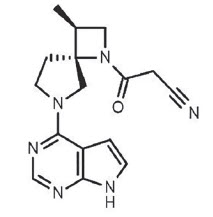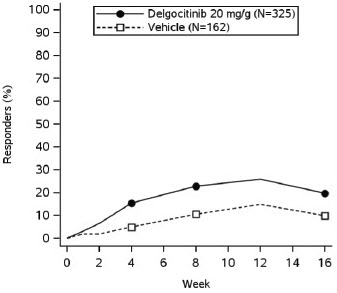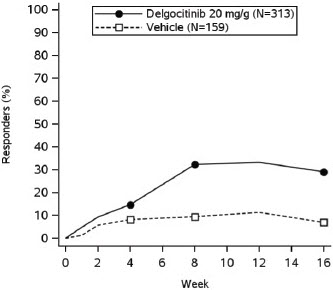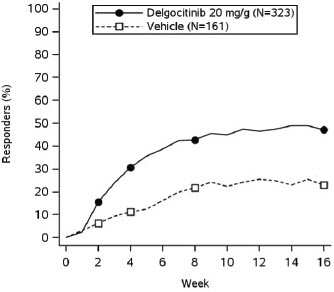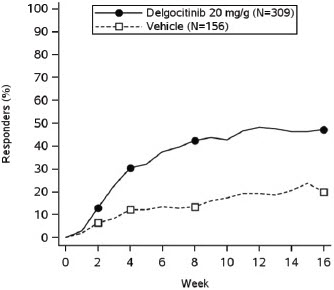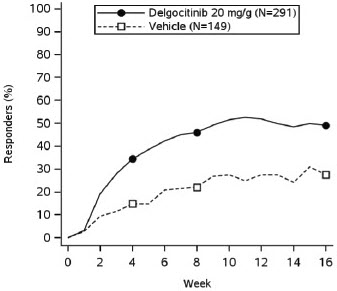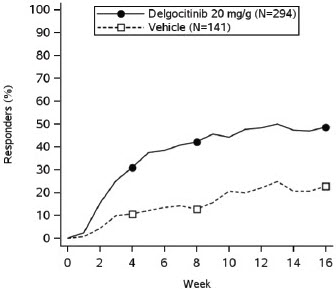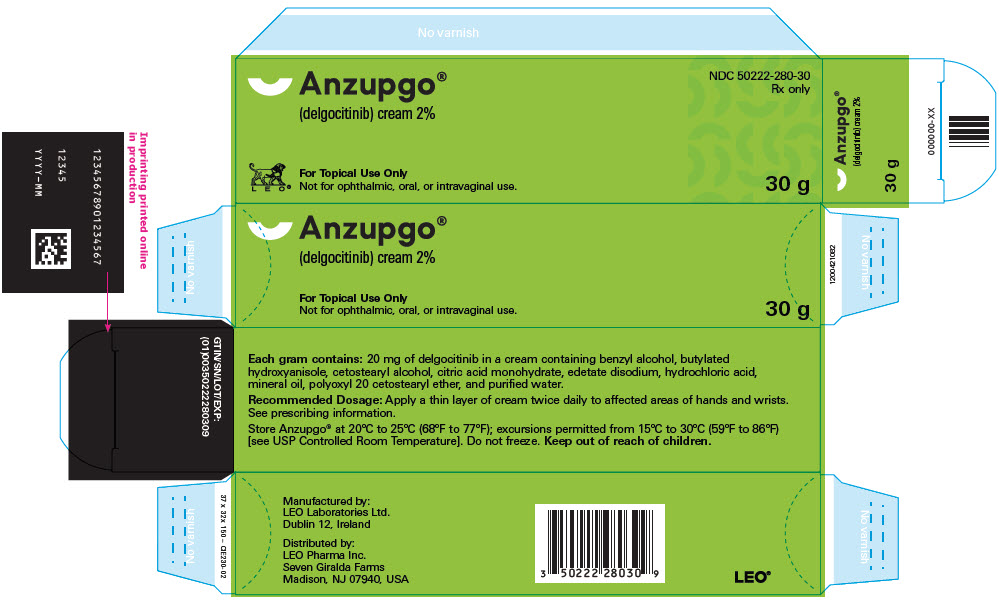 DRUG LABEL: Anzupgo
NDC: 50222-280 | Form: CREAM
Manufacturer: LEO Pharma, Inc
Category: prescription | Type: HUMAN PRESCRIPTION DRUG LABEL
Date: 20250728

ACTIVE INGREDIENTS: DELGOCITINIB 20 mg/1 g
INACTIVE INGREDIENTS: BENZYL ALCOHOL; BUTYLATED HYDROXYANISOLE; CETOSTEARYL ALCOHOL; CITRIC ACID MONOHYDRATE; EDETATE DISODIUM; HYDROCHLORIC ACID; MINERAL OIL; POLYOXYL 20 CETOSTEARYL ETHER; WATER

HIGHLIGHTS OF PRESCRIBING INFORMATION

These highlights do not include all the information needed to use ANZUPGO® safely and effectively. See full prescribing information for ANZUPGO®.
ANZUPGO® (delgocitinib) cream, for topical use
Initial U.S. Approval: 2025

1 INDICATIONS AND USAGE

ANZUPGO is a Janus kinase (JAK) inhibitor indicated for the topical treatment of moderate to severe chronic hand eczema (CHE) in adults who have had an inadequate response to, or for whom topical corticosteroids are not advisable. (1)

Limitations of Use: Use of ANZUPGO in combination with other JAK inhibitors or potent immunosuppressants is not recommended. (1)

2 DOSAGE AND ADMINISTRATION

- See the full prescribing information for recommended immunizations prior to treatment. (2.1)
- Do not use more than 30 grams per 2 weeks or 60 grams per month.
- Apply twice daily to skin of the affected areas only on the hands and wrists. (2.2)
- For topical use only. Not for oral, ophthalmic, or intravaginal use. (2.2)

3 DOSAGE FORMS AND STRENGTHS

Cream: Each gram of ANZUPGO cream contains 20 mg of delgocitinib. (3)

4 CONTRAINDICATIONS

None. (4)

5 WARNINGS AND PRECAUTIONS

- Serious Infections: ANZUPGO may increase the risk of infection. Eczema herpeticum was observed in a subject treated topically with ANZUPGO. Avoid use of ANZUPGO in patients with an active or serious infection. If a serious infection develops, discontinue ANZUPGO until the infection resolves. (5.1)
- Non-melanoma Skin Cancers: Non-melanoma skin cancers including basal cell carcinoma have been reported in subjects treated with ANZUPGO. Periodic skin examinations are recommended for all patients, particularly those with risk factors for skin cancer. (5.2)
- Immunizations: Avoid vaccination with live vaccines immediately prior to, during, and immediately after ANZUPGO treatment. (5.3)
- Potential Risks Related to JAK Inhibition: It is not known whether ANZUPGO may be associated with the observed or potential adverse reactions of JAK inhibition. Higher rates of all-cause mortality, including sudden cardiovascular death, major adverse cardiovascular events, overall thrombosis, deep venous thrombosis, pulmonary embolism, and malignancies (excluding non-melanoma skin cancer) were observed in patients treated with a JAK inhibitor compared to those treated with TNF blockers in rheumatoid arthritis (RA) patients. ANZUPGO is not approved for use in RA. Treatment with oral and topical JAK inhibitors has been associated with increases in lipid parameters including total cholesterol, low-density lipoprotein (LDL) cholesterol, and triglycerides. (5.4)

6 ADVERSE REACTIONS

Adverse reactions that were reported in ≤ 1% of subjects were application site pain, paresthesia, pruritus, erythema, and bacterial skin infections including finger cellulitis, paronychia, other skin infections, leukopenia, and neutropenia. (6.1)

To report SUSPECTED ADVERSE REACTIONS, contact LEO Pharma Inc. at 1-877-494-4536 or FDA at 1-800-FDA-1088 or www.fda.gov/medwatch.

FULL PRESCRIBING INFORMATION

1 INDICATIONS AND USAGE

ANZUPGO is indicated for the topical treatment of moderate to severe chronic hand eczema (CHE) in adults who have had an inadequate response to, or for whom topical corticosteroids are not advisable.

Limitations of Use

Use of ANZUPGO in combination with other JAK inhibitors or potent immunosuppressants is not recommended.

2 DOSAGE AND ADMINISTRATION

2.1 Recommended Immunizations Prior to Treatment Initiation

Complete any necessary immunizations, including herpes zoster vaccinations, according to current immunization guidelines prior to ANZUPGO treatment [see Warnings and Precautions (5.3)].

2.2 Recommended Dosage and Administration

Do not use more than 30 grams per 2 weeks or 60 grams per month.

Prior to applying ANZUPGO, clean and dry affected areas.

Apply a thin layer of ANZUPGO, twice daily, to the affected areas only on the hands and wrists.

ANZUPGO is for topical use only. Not for oral, ophthalmic, or intravaginal use.

Avoid contact with eyes, mouth, or other mucous membranes. If contact with mucous membranes occurs, rinse thoroughly with water.

3 DOSAGE FORMS AND STRENGTHS

Cream, 2%: Each gram of ANZUPGO cream contains 20 mg of delgocitinib in a white to slightly brown cream.

4 CONTRAINDICATIONS

None

5 WARNINGS AND PRECAUTIONS

5.1 Serious Infections

ANZUPGO may increase the risk of infections. Eczema herpeticum was observed in a subject treated with ANZUPGO [see Adverse Reactions (6.1)]. Serious and sometimes fatal infections due to bacterial, mycobacterial, invasive fungal, viral, or other opportunistic pathogens have been reported in patients receiving oral or topical JAK inhibitors [see Adverse Reactions (6.1)].

Avoid use of ANZUPGO in patients with an active or serious infection.

Consider the risks and benefits of treatment prior to initiating ANZUPGO in patients:

- with chronic or recurrent infection
- who have been exposed to tuberculosis
- with a history of a serious or an opportunistic infection
- with underlying conditions that may predispose them to infection.

Closely monitor patients for the development of signs and symptoms of infection during and after treatment with ANZUPGO. A patient who develops a new infection during treatment with ANZUPGO should undergo prompt and complete diagnostic testing; appropriate antimicrobial therapy should be initiated; and the patient should be closely monitored. Interrupt treatment with ANZUPGO if a patient develops a serious infection. Do not resume ANZUPGO until the infection resolves or is adequately treated.

Viral Reactivation

Viral reactivation, including cases of herpes virus reactivation (e.g., herpes zoster), were reported in clinical trials with ANZUPGO. If a patient develops herpes zoster, consider interrupting ANZUPGO treatment until the episode resolves.

The impact of ANZUPGO on chronic viral hepatitis reactivation is unknown. Patients with active hepatitis B or C infection were excluded from clinical trials with ANZUPGO. Consider viral hepatitis screening and monitoring for reactivation in accordance with clinical guidelines before starting therapy and during therapy with ANZUPGO. If signs of reactivation occur, consult a hepatitis specialist. ANZUPGO is not recommended for use in patients with active hepatitis B or hepatitis C.

5.2 Non-melanoma Skin Cancers

Non-melanoma skin cancers including basal cell carcinoma have been reported in subjects treated with ANZUPGO. Periodic skin examinations of the application sites are recommended for all patients, particularly those with risk factors for skin cancer. Advise patients to avoid sunlamps and minimize exposure to sunlight by wearing sun-protective clothing or using broad-spectrum sunscreen.

5.3 Immunizations

Prior to ANZUPGO treatment, complete all age-appropriate vaccinations as recommended by current immunization guidelines, including herpes zoster vaccinations. Avoid vaccination with live vaccines immediately prior to, during, and immediately after ANZUPGO treatment.

5.4 Potential Risks Related to JAK Inhibition

It is not known whether ANZUPGO may be associated with the observed or potential adverse reactions of JAK inhibition.

In a large, randomized, postmarketing safety trial of an oral JAK inhibitor in combination with methotrexate in rheumatoid arthritis (RA), patients 50 years of age and older with at least one cardiovascular risk factor, higher rates of all-cause mortality, including sudden cardiovascular death, major adverse cardiovascular events (MACE), overall thrombosis, deep venous thrombosis (DVT), pulmonary embolism (PE), and malignancies (excluding non-melanoma skin cancer) were observed in patients treated with the JAK inhibitor compared to those treated with TNF blockers. ANZUPGO is not indicated for use in RA.

Treatment with oral and topical JAK inhibitors has been associated with increases in lipid parameters including total cholesterol, low-density lipoprotein (LDL) cholesterol, and triglycerides.

6 ADVERSE REACTIONS

6.1 Clinical Trials Experience

Because clinical trials are conducted under widely varying conditions, adverse reaction rates observed in the clinical trials of a drug cannot be directly compared to rates in the clinical trials of another drug and may not reflect the rates observed in clinical practice.

The safety of ANZUPGO was evaluated in two randomized, double-blind, multicenter, vehicle-controlled clinical trials (TRIAL 1 and TRIAL 2), in which 959 adults with moderate to severe CHE received ANZUPGO or vehicle cream topically twice daily for 16 weeks. A total of 638 subjects were treated with ANZUPGO [see Clinical Studies (14)].

In TRIAL 1 and TRIAL 2, adverse reactions that were reported in ≤ 1% of subjects in the ANZUPGO group were application site pain, paresthesia, pruritus, erythema, and bacterial skin infections including finger cellulitis, paronychia, other skin infections, leukopenia, and neutropenia.

In an open label extension trial (TRIAL 3), 801 subjects were treated for up to an additional 36 weeks after completing TRIAL 1 or TRIAL 2. A total of 198 subjects received continuous treatment with ANZUPGO for 52 weeks. Eczema herpeticum was observed in one subject and herpes zoster was observed in two subjects treated with ANZUPGO.

8 USE IN SPECIFIC POPULATIONS

8.1 Pregnancy

Risk Summary

The available data on the use of topical delgocitinib during pregnancy is insufficient to evaluate for a drug-associated risk of major birth defects, miscarriage, or other adverse maternal or fetal outcomes.

In animal reproduction studies, oral administration of delgocitinib to pregnant rats and rabbits during the period of organogenesis did not result in adverse developmental effects at doses 120 or 193 times, respectively, the maximum recommended human dose (MRHD) based on AUC comparison (see Data).

The background risk of major birth defects and miscarriage for the indicated population is unknown. All pregnancies have a background risk of birth defects, loss, and other adverse outcomes. In the U.S. general population, the estimated background risk of major birth defects and miscarriage in clinically recognized pregnancies is 2%-4% and 15%-20%, respectively.

Data

Animal Data

In embryofetal development studies, delgocitinib was administered orally to pregnant rats or rabbits during the period of organogenesis at doses of 3, 10 and 30 mg/kg/day in rats, and 1, 3 and 10 mg/kg/day in rabbits, respectively.

In rats, no significant maternal toxicity was noted at doses up to 30 mg/kg/day (1446 times the MRHD based on AUC comparison). Decreases in fetal weight and skeletal variations were observed at doses ≥10 mg/kg/day (512 times the MRHD based on AUC comparison). An increase in post-implantation loss was observed at 30 mg/kg/day (1446 times the MRHD based on AUC comparison). No embryofetal toxicity was noted at 3 mg/kg/day (120 times the MRHD based on AUC comparison).

In rabbits, no significant maternal toxicity was noted at doses up to 10 mg/kg/day (992 times the MRHD based on AUC comparison). An increase in post-implantation loss, reduced number of live fetuses, and decrease in fetal weights were observed at 10 mg/kg/day (992 times the MRHD based on AUC comparison). No embryofetal toxicity was noted at 3 mg/kg/day (193 times the MRHD based on AUC comparison).

In a pre- and post-natal development study in pregnant rats, delgocitinib was orally administered at doses of 3, 10 and 30 mg/kg/day from gestation day 7 to lactation day 20. No significant maternal toxicity was noted at 30 mg/kg/day (1555 times the MRHD based on AUC comparison). Extended gestation period, a decrease in the birth index, and an increase in the number of dead newborns were observed at 30 mg/kg/day (1555 times the MRHD based on AUC comparison). Decreased fetal viability and reduced pup weights were noted during the early postnatal period at 30 mg/kg/day (1555 times the MRHD based on AUC comparison).

No developmental toxicity was noted at 10 mg/kg/day (378 times the MRHD based on AUC comparison).

8.2 Lactation

Risk Summary

There are no data on the presence of delgocitinib in human milk, the effects on the breastfed infant, or the effects on milk production. After oral administration, delgocitinib was present in the milk of lactating rats. When a drug is present in animal milk, it is likely that the drug will be present in human milk. The developmental and health benefits of breastfeeding should be considered along with the mother's clinical need for ANZUPGO and any potential adverse effects on the breastfed infant from ANZUPGO or from the underlying maternal condition.

Clinical Considerations

To minimize potential infant exposure, advise breastfeeding women to avoid direct contact with the nipple and surrounding area immediately after applying ANZUPGO to the hands and/or wrists.

8.4 Pediatric Use

The safety and efficacy of ANZUPGO have not been established in pediatric patients.

8.5 Geriatric Use

Of the 691 subjects exposed to ANZUPGO in clinical trials, 59 subjects (8.5%) were 65 years of age and older and 10 subjects (1.4%) were 75 years of age and older. No overall differences in safety or effectiveness were observed between subjects 65 years of age and older and younger adult subjects.

11 DESCRIPTION

ANZUPGO (delgocitinib) cream is a white to slightly brown cream for topical use and contains delgocitinib as the active ingredient.

Delgocitinib is a white to almost white powder. Delgocitinib is slightly soluble in aqueous solutions at pH 5.0. The pKa of delgocitinib is 5.5.

Delgocitinib is a Janus kinase (JAK) inhibitor [JAK1, JAK2, JAK3, and tyrosine kinase 2 (TYK2)] with the chemical name 3-[(3S,4R)-3-Methyl- 6-(7H-pyrrolo[2,3-d]pyrimidin-4-yl)-1,6-diazaspiro[3.4]octan-1-yl]-3- oxopropanenitrile.

The molecular formula is C16H18N6O and the molecular weight is 310.35 g/mol. Delgocitinib has the structural formula:

Each gram of ANZUPGO contains 20 mg of delgocitinib. Inactive ingredients include benzyl alcohol, butylated hydroxyanisole, cetostearyl alcohol, citric acid monohydrate, edetate disodium, hydrochloric acid, mineral oil, polyoxyl 20 cetostearyl ether, and purified water.

12 CLINICAL PHARMACOLOGY

12.1 Mechanism of Action

Delgocitinib, a Janus kinase (JAK) inhibitor, inhibits the activity of JAK1, JAK2, JAK3, and tyrosine kinase 2 (TYK2). JAK signaling involves recruitment of signal transducers and activators of transcription (STATs) to cytokine receptors, and activation and subsequent localization of STATs to the nucleus, leading to the expression of cytokine-responsive genes to induce specific biological responses in target cells. The exact mechanism of action of delgocitinib in the treatment of moderate to severe CHE is currently not known.

12.2 Pharmacodynamics

Pharmacodynamics of delgocitinib in the treatment of CHE are unknown.

Cardiac Electrophysiology

At 193 times the mean maximal concentration provided by the recommended topical dose, clinically significant QTc interval prolongation was not observed.

12.3 Pharmacokinetics

The pharmacokinetics of ANZUPGO were evaluated in a pharmacokinetic (PK) trial involving 15 adult subjects 22 to 69 years of age with moderate to severe CHE and in 313 subjects in TRIAL 2 [see Clinical Studies (14)].

Absorption

In the PK trial, subjects applied on average 0.87 g of ANZUPGO topically to the affected areas of the hands and wrists twice a day for 8 days.

The mean ± SD maximum plasma concentration (Cmax) and area under the concentration-curve from time 0 to 12 hours (AUC0-12) on Day 1 was 1.53 ng/mL ± 2.24 and 6.1 ng*h/mL ± 8.14, respectively. The lower limit of quantification was 0.005 ng/mL in the assay. The systemic exposure (AUC and Cmax) between Day 1 and Day 8 were similar. There was no evidence of accumulation with twice daily topical application of ANZUPGO.

In TRIAL 2, a single PK sample was assessed between 2-6 hours following twice daily application of ANZUPGO. The mean plasma concentration on Weeks 1, 4, and 16 were 0.42 ng/mL, 0.50 ng/mL, and 0.35 ng/mL, respectively.

Distribution

Plasma protein binding of delgocitinib is 22 to 29%.

Elimination

Following repeated topical application of ANZUPGO, the average half-life of delgocitinib was estimated to be 21 hours.

Metabolism

Delgocitinib does not undergo extensive metabolism and the main plasma component is unchanged delgocitinib. Following oral administration, four metabolites (formed via oxidation and glucuronide conjugation) were detected at < 2% of the average unchanged delgocitinib plasma concentrations. The limited metabolism of delgocitinib occurs primarily though CYP3A4/5 and to a lesser extent by CYP1A1, CYP2C9, CYP2C19, and CYP2D6.

Excretion

Delgocitinib is primarily eliminated by renal excretion as approximately 75% of the total dose after oral administration was found unchanged in the urine.

Drug Interaction Studies

Clinical Studies

Drug interaction studies with ANZUPGO have not been conducted.

In Vitro Studies

Delgocitinib does not inhibit or induce cytochrome P450 enzymes or inhibit transporter systems such as P-glycoprotein (P-gp), breast cancer resistance protein (BCRP), organic anion transporting proteins (OATP), organic anion transporters (OAT), organic cation transporters (OCT), or multidrug and toxin extrusion protein (MATE) at clinically relevant concentrations.

13 NONCLINICAL TOXICOLOGY

13.1 Carcinogenesis, Mutagenesis, Impairment of Fertility

Delgocitinib was not carcinogenic when administered topically in a 2-year dermal carcinogenicity study in mice. No drug-related neoplastic findings were observed at strengths up to 5% delgocitinib ointment (approximately 600 times the MRHD based on AUC comparison). In a 2-year oral carcinogenicity study in rats, delgocitinib was administered at doses of 3, 10, and 30 mg/kg/day. Benign thymoma was seen in female rats at 30 mg/kg/day (2274 times the MRHD based on AUC comparison). No drug-related neoplastic findings were observed in males at doses up to 30 mg/kg/day (1869 times the MRHD based on AUC comparison) or in females at 10 mg/kg/day (580 times the MRHD based on AUC comparison).

Delgocitinib was not mutagenic or clastogenic in a bacterial mutagenicity assay (the Ames test) or in vivo chromosomal aberration tests in rat bone marrow cells and human peripheral blood lymphocytes. Delgocitinib did not impair fertility in male rats at oral doses up to 30 mg/kg/day (1308 times the MRHD based on AUC comparison). In female rats, delgocitinib resulted in a decrease in fertility index and corpora lutea, and an increase in implantation loss at 100 mg/kg/day (5897 times the MRHD based on AUC comparison). An increase in post-implantation loss and a decrease in the number of live embryos were observed at 10 and 30 mg/kg/day, respectively (432 and 1087 times the MRHD based on AUC comparison). No adverse effects on fertility were noted at 30 mg/kg/day (1087 times the MRHD based on AUC comparison) and no adverse effects on early embryonic development were noted at 3 mg/kg/day (110 times the MRHD based on AUC comparison).

14 CLINICAL STUDIES

The efficacy of ANZUPGO was evaluated in two randomized, double-blind, vehicle-controlled, 16-week trials (TRIAL 1 [NCT04871711] and TRIAL 2 [NCT04872101]) which enrolled a total of 960 adult subjects with moderate to severe CHE who had a history of inadequate response to, or for whom topical corticosteroids were not advisable. All subjects who completed TRIAL 1 and TRIAL 2 were eligible to enroll into a long-term extension trial (TRIAL 3 [NCT04949841]).

Disease severity of enrolled subjects was defined using the Investigator's Global Assessment for chronic hand eczema (IGA-CHE) score and the Hand Eczema Symptom Diary (HESD) itch score (weekly average). The IGA-CHE is the investigator's overall assessment of chronic hand eczema at a given time point on a scale ranging from 0 (clear) to 4 (severe). The HESD itch score assesses disease severity of pruritus using a scale ranging from 0 (no symptoms) to 10 (severe symptoms). Subjects enrolled in these three trials had an IGA-CHE score of 3 or 4 (moderate or severe, respectively) and a HESD itch score (weekly average) of ≥ 4 points at baseline.

Across all treatment groups in TRIAL 1 and TRIAL 2, the mean age of enrolled subjects was 44.1 years, and 8% of subjects were 65 years of age or older, 64% were female, 90% were White, 4% were Asian, and 1% were Black. For ethnicity, 94% of subjects identified as not Hispanic or Latino and 3% of subjects identified as Hispanic or Latino. The primary classifications of CHE by subtype were atopic hand eczema (35.9%), hyperkeratotic eczema (21.5%), irritant contact dermatitis (19.6%), allergic contact dermatitis (13.9%), vesicular hand eczema (9.1%), and contact urticaria/protein contact dermatitis (0.1%). Across all trial arms, 28% of subjects were diagnosed with two or more overlapping CHE subtypes.

The HESD itch score is a weekly average of daily itch severity on an 11-point scale from 0-10 that assesses the maximal intensity of pruritus in the last 24 hours with 0 being no pruritus and 10 being the worst pruritus. The HESD pain score is a weekly average of daily pain severity on an 11-point scale from 0-10 that assesses the maximal intensity of pain in the last 24 hours with 0 being no pain and 10 being the worst pain. In these trials, 28% of subjects had a baseline IGA-CHE score of 4 (severe CHE). The mean baseline HESD itch and pain scores were 7.1 and 6.7, respectively.

In both trials, subjects applied either topical ANZUPGO or vehicle twice daily to affected areas on the hands and wrists for 16 weeks. The primary efficacy endpoint was the proportion of subjects who achieved IGA-CHE treatment success (IGA-CHE TS) at Week 16, defined as a score of 0 (clear) or 1 (almost clear) with at least a 2-point improvement from baseline. Table 2 describes the efficacy results at Week 16 in TRIAL 2. Figure 1 describes the proportion of subjects who achieve IGA-CHE TS during the 16-week treatment period in TRIAL 1 and TRIAL 2. Figures 2 and 3 describe the proportion of subjects who achieved HESD itch ≥ 4-point improvement and HESD pain ≥ 4-point improvement during the 16-week treatment period in TRIAL 1 and TRIAL 2.

Table 1: Efficacy Results of ANZUPGO in Adults with Moderate to Severe CHE at Week 16 in TRIAL 1 and TRIAL 2
 | TRIAL 1 |  | TRIAL 2
 | ANZUPGO (N=325) | Vehicle (N=162) | ANZUPGO (N=313) | Vehicle (N=159)
IGA-CHE TS, % responders [Data after initiation of rescue treatment, permanent discontinuation of treatment, or missing data were considered non-response.] , [IGA-CHE treatment success (IGA-CHE TS) was defined as a score of 0 (clear) or 1 (almost clear) with at least a 2-point improvement from baseline.] | 20% (64/325) | 10% (16/162) | 29% (91/313) | 7% (11/159)
Difference from Vehicle (95% CI) | 10% (4%, 16%) |  | 22% (16%, 29%)
HESD itch ≥ 4-point improvement, % responders, [Based on the number of subjects whose weekly average baseline value was ≥ 4 (scale from 0-10).] | 47% (152/323) | 23% (37/161) | 47% (146/309) | 20% (31/156)
Difference from Vehicle (95% CI) | 24% (16%, 33%) |  | 27% (19%, 36%)
HESD pain ≥ 4-point improvement, % responders, | 49% (143/291) | 28% (41/149) | 49% (143/294) | 23% (32/141)
Difference from Vehicle (95% CI) | 22% (12%, 31%) |  | 26% (17%, 35%)
Abbreviations: N=number of subjects in the full analysis set (all subjects randomized and dosed);

Figure 1: Proportion of Adult Subjects with Moderate to Severe CHE who Achieved IGA-CHE Treatment Success (0 or 1 with ≥2-point improvement from baseline) Over Time in TRIAL 1 and TRIAL 2

TRIAL 1

TRIAL 2

Point symbols are the multiplicity controlled timepoints.

Figure 2: Proportion of Adult Subjects with Moderate to Severe CHE who Achieved HESD Itch ≥ 4-point Improvement Over Time in TRIAL 1 and TRIAL 2

TRIAL 1

TRIAL 2

Based on the number of subjects whose weekly average baseline value was ≥ 4 (scale from 0-10).

Point symbols are the multiplicity controlled timepoints.

Figure 3: Proportion of Adult Subjects with Moderate to Severe CHE who Achieved HESD Pain ≥ 4-point Improvement Over Time in TRIAL 1 and TRIAL 2

TRIAL 1

TRIAL 2

Based on the number of subjects whose weekly average baseline value was ≥ 4 (scale from 0-10).

Point symbols are the multiplicity controlled timepoints.

16 HOW SUPPLIED/STORAGE AND HANDLING

How Supplied

ANZUPGO is a white to slightly brown cream containing 2% delgocitinib (each gram contains 20 mg of delgocitinib) and is supplied in the following package:

- 30 g laminated tubes: NDC 50222-280-30

Storage and Handling

Store ANZUPGO at 20°C to 25°C (68°F to 77°F); excursions permitted from 15°C to 30°C (59°F to 86°F) [see USP Controlled Room Temperature]. Do not freeze.

17 PATIENT COUNSELING INFORMATION

Advise patients to read the FDA-approved patient labeling (Patient Information).

Administration Instructions

Advise patients that ANZUPGO is for topical use only and is not for ophthalmic, oral, or intravaginal use [see Dosage and Administration (2.2)].

Advise patients to limit treatment to 30 grams per 2 weeks or 60 grams per month. [see Dosage and Administration (2.2)].

Instruct patients to clean and dry affected areas prior to applying ANZUPGO. Instruct patients to apply ANZUPGO, twice daily, to affected areas only on the hands and wrists, and avoid contact with eyes, mouth, or other mucous membranes [see Dosage and Administration (2.2)].

Serious Infections

Inform patients that ANZUPGO may lower the ability of their immune system to fight infections and to contact their healthcare provider immediately if they develop any signs or symptoms of infection [see Warnings and Precautions (5.1)].

Non-melanoma Skin Cancers

Inform patients that ANZUPGO may increase the risk of developing non-melanoma skin cancers. Inform patients that periodic skin examinations should be performed while using ANZUPGO. Instruct patients to inform their healthcare provider if they have ever had any type of cancer. Advise patients to avoid sunlamps and minimize exposure to sunlight by wearing sun-protective clothing or using broad-spectrum sunscreen [see Warnings and Precautions (5.2)].

Immunizations

Advise patients treated with ANZUPGO to avoid use of live vaccines immediately prior to, during, and immediately after treatment [see Warnings and Precautions (5.3)].

Lactation

Advise breastfeeding women to avoid direct contact with the nipple and surrounding area immediately after applying ANZUPGO to the hands and/ or wrists to minimize infant exposure [see Use in Specific Populations (8.2)].

Manufactured by:
LEO Laboratories Ltd.
285 Cashel Road
Dublin 12, Ireland

Distributed by:
LEO Pharma Inc.
Madison, NJ 07940, USA

ANZUPGO® is a registered trademark of LEO Pharma A/S.
© 2025 LEO Pharma Inc. All rights reserved.

MEDICATION GUIDE ANZUPGO® (an zup goe) (delgocitinib) cream

Important: ANZUPGO is for use on the skin (topical use) only. Do not use ANZUPGO in or on your eyes, mouth, or vagina.

What is the most important information I should know about ANZUPGO?

ANZUPGO may cause serious side effects, including:

- Serious Infections. ANZUPGO may increase your risk of infections. ANZUPGO contains delgocitinib. Delgocitinib belongs to a class of medicines called Janus kinase (JAK) inhibitors. JAK inhibitors are medicines that affect your immune system. JAK inhibitors can lower the ability of your immune system to fight infections. Some people have had serious infections while taking JAK inhibitors by mouth or applying on the skin, including tuberculosis (TB), and infections caused by bacteria, fungi, or viruses that can spread throughout the body. Some people have been hospitalized or died from these infections.
  - ANZUPGO should not be used in people with an active, serious infection. You should not start using ANZUPGO if you have any kind of infection unless your healthcare provider tells you it is okay. You may be at a higher risk of developing shingles (herpes zoster) or eczema herpeticum (a blistery, painful skin rash) during treatment with ANZUPGO.
  Before starting ANZUPGO, tell your healthcare provider if you:
  - are being treated for an infection
  - have an infection that does not go away or that keeps coming back
  - have TB or have been in close contact with someone with TB
  - have had shingles (herpes zoster)
  - have had hepatitis B or C
  - think you have an infection or have symptoms of an infection such as:
    - fever, sweating, or chills
    - muscle aches
    - cough or shortness of breath
    - blood in your phlegm
    - weight loss
    - warm, red, or painful skin or sores on your body
    - diarrhea or stomach pain
    - burning when you urinate or
    - urinating more often than usual
    - feeling very tired
  After starting ANZUPGO, call your healthcare provider right away if you have any symptoms of an infection.
  ANZUPGO can make you more likely to get infections or make worse any infections that you have. If you get a serious infection, your healthcare provider may stop your treatment with ANZUPGO until your infection is controlled.
- Non-melanoma skin cancer. ANZUPGO may increase your risk of certain non-melanoma skin cancers. Your healthcare provider will regularly check your skin during your treatment with ANZUPGO.
  - Avoid sunlamps and limit the amount of time you spend in the sunlight. Wear protective clothing when you are in the sun or use a broad-spectrum sunscreen.
  - Tell your healthcare provider if you have ever had any type of cancer.
- Potential risks from Janus kinase (JAK) inhibition. It is not known whether using ANZUPGO has the same risks as taking other oral or topical JAK inhibitors. Increased risk of death (all causes) has happened in people who were 50 years of age and older with at least 1 heart disease (cardiovascular) risk factor who were taking a JAK inhibitor used to treat rheumatoid arthritis (RA) compared to people taking another medicine in a class of medicines called TNF blockers. ANZUPGO is not for use in people with RA. Other oral or topical JAK inhibitors have also caused increased cholesterol.

See "What are the possible side effects of ANZUPGO?" for more information about side effects.

What is ANZUPGO?

ANZUPGO is a prescription medicine used on the skin (topical) to treat moderate to severe chronic hand eczema in adults who are not well-controlled with, or cannot use topical corticosteroids.

The use of ANZUPGO along with other JAK inhibitors or strong immunosuppressants is not recommended.

It is not known if ANZUPGO is safe and effective in children.

Before using ANZUPGO, tell your healthcare provider about all your medical conditions, including if you:

- See "What is the most important information I should know about ANZUPGO?"
- have an infection
- have recently received or are scheduled to receive a vaccine. People who use ANZUPGO should not receive live vaccines right before starting, during treatment, or right after treatment with ANZUPGO.
- are pregnant or plan to become pregnant. It is not known if ANZUPGO will harm your unborn baby.
- are breastfeeding or plan to breastfeed. It is not known if ANZUPGO passes into your breast milk. Talk to your healthcare provider about the best way to feed your baby during treatment with ANZUPGO.
  If you use ANZUPGO while breastfeeding, avoid touching the nipple and surrounding area right away after applying ANZUPGO to your hands and wrists.

Tell your healthcare provider about all of the medicines you take, including prescription and over-the-counter medicines, vitamins, and herbal supplements.

How should I use ANZUPGO?

- ANZUPGO is for use on the skin of your hands and wrists only. Do not use ANZUPGO in or on your eyes, mouth, vagina or other mucous membranes. If contact with mucous membranes happens, rinse well with water.
- Use ANZUPGO exactly as your healthcare provider tells you to use it.
- Clean and dry skin of the affected areas before applying ANZUPGO.
- Apply a thin layer of ANZUPGO 2 times each day to affected areas on your hands and wrists. Do not use more than 30 grams in 2 weeks or 60 grams in a month.
- If someone else applies ANZUPGO for you, they should wash their hands after applying ANZUPGO.

What are the possible side effects of ANZUPGO?

ANZUPGO may cause serious side effects, including:

- See "What is the most important information I should know about ANZUPGO?"

The most common side effects of ANZUPGO include:

- application site reactions, including pain, tingling, itching, and redness
- bacterial skin infections, including finger cellulitis, and nail infections
- low white blood cells

These are not all of the possible side effects of ANZUPGO.

Call your doctor for medical advice about side effects. You may report side effects to FDA at 1-800-FDA-1088.

How should I store ANZUPGO?

- Store ANZUPGO at room temperature between 68°F to 77°F (20°C to 25°C).
- Do not freeze ANZUPGO.

Keep ANZUPGO and all medicines out of the reach of children.

General information about the safe and effective use of ANZUPGO.

Medicines are sometimes prescribed for purposes other than those listed in a Medication Guide. Do not use ANZUPGO for a condition for which it was not prescribed. Do not give ANZUPGO to other people, even if they have the same symptoms you have. It may harm them. You can ask your pharmacist or healthcare provider for information about ANZUPGO that is written for health professionals.

What are the ingredients in ANZUPGO?

Active ingredient: delgocitinib

Inactive ingredients: benzyl alcohol, butylated hydroxyanisole, cetostearyl alcohol, citric acid monohydrate, edetate disodium, hydrochloric acid, mineral oil, polyoxyl 20 cetostearyl ether, and purified water.

Manufactured by:
LEO Laboratories Ltd., 285 Cashel Road, Dublin 12, Ireland

Distributed by:
LEO Pharma Inc., Madison, NJ 07940, USA

ANZUPGO® is a registered trademark of LEO Pharma A/S.
© 2025 LEO Pharma Inc. All rights reserved.

For more information about ANZUPGO, go to www.ANZUPGO.com or call 1-877-494-4536.

This Medication Guide has been approved by the U.S. Food and Drug Administration.

Issued: 7/2025

LEO®

075997

PRINCIPAL DISPLAY PANEL - 30 g Tube Carton

Anzupgo®
(delgocitinib) cream 2%

LEO®

For Topical Use Only
Not for ophthalmic, oral, or intravaginal use.

NDC 50222-280-30
Rx only

30 g